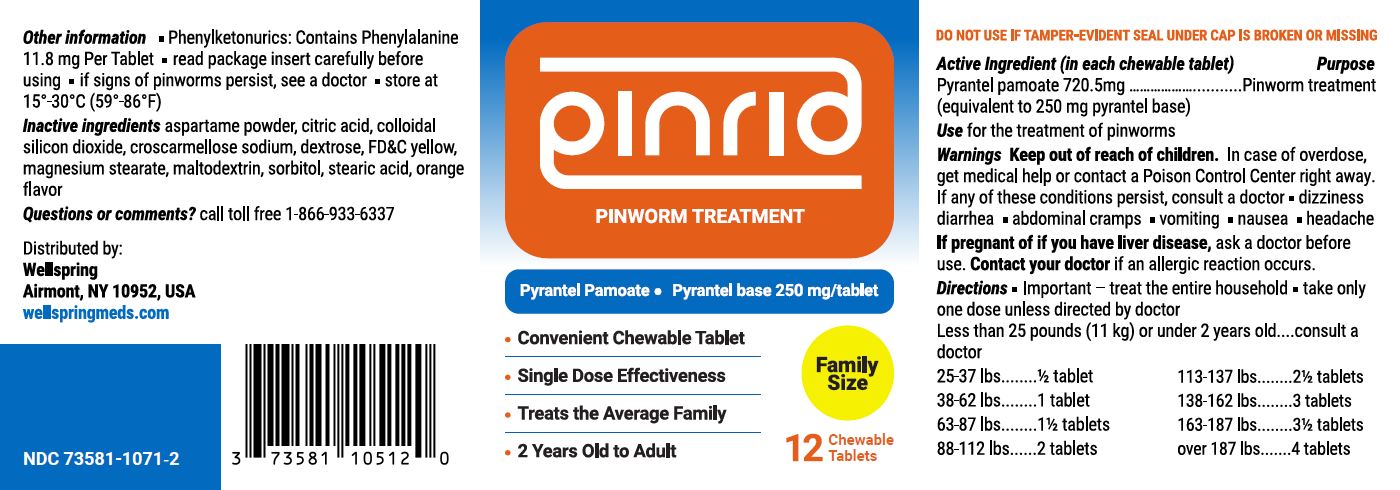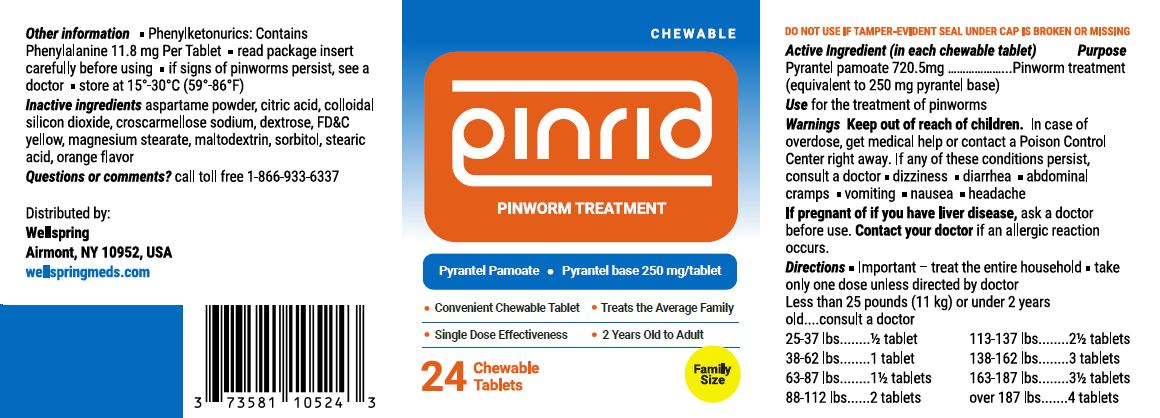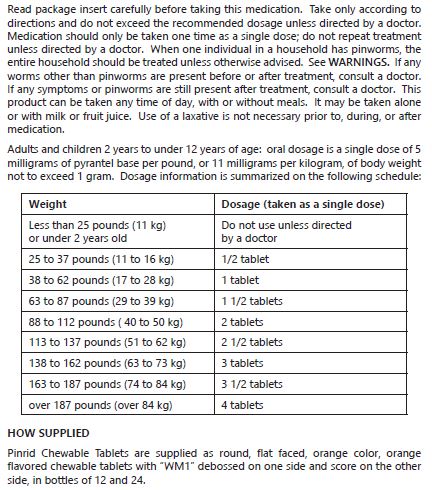 DRUG LABEL: PINRID
NDC: 73581-107 | Form: TABLET
Manufacturer: YYBA CORP
Category: otc | Type: HUMAN OTC DRUG LABEL
Date: 20240103

ACTIVE INGREDIENTS: PYRANTEL PAMOATE 250 mg/1 1
INACTIVE INGREDIENTS: ASPARTAME; ANHYDROUS CITRIC ACID; SILICON DIOXIDE; CROSCARMELLOSE SODIUM; DEXTROSE; FD&C YELLOW NO. 5; MAGNESIUM STEARATE; MALTODEXTRIN; SORBITOL; STEARIC ACID

YYBA (as PLD) - PINRID (TABLET) (73581-107)

ACTIVE INGREDIENT

PYRANTEL PAMOATE 720.5 MG

PURPOSE

PINROOM TREATMENT

USE

FOR THE TREATMENT OF PINWORMS

WARNINGS

IF ANY OF THESE CONDITIONS PERSIST, CONSULT A DOCTOR

- DIZZINESS
- DIARHEA
- ABDOMINAL CRAMPS
- VOMITING
- NAUSEA
- HEADACHE

IF PREGNANT OR IF YOU HAVE LIVER DISEASE, ASK A DOCTOR BEFORE USE. CONSULT YOUR DOCTOR IF AN ALLERGIC REACTION OCCURS.

KEEP OUT OF REACH OF CHILDREN. IN CASE OF ACCIDENTAL OVERDOSE, GET MEDICAL HELP OR CONTACT A POISON CONTROL CENTER RIGHT AWAY.

OTHER INFORMATION

- PHENYLKETONURICS: CONTAIN PHENYLALANINE 11.8 MG PER TABLET
- READ PACKAGE INSERT CAREFULLY BEFORE USING
- IF SIGNS OF PINWORMS PERSIST, SEE A DOCTOR
- STORE AT 15° - 30°c (59° - 86°f)

INACTIVE INGREDIENTS

aspartame powder, citric acid, colloidal silicon dioxide, croscarmellose sodium, dextrose, FD&C yellow, magnesium stearate, maltodextrin, sorbitol, stearic acid, orange fl avor.

QUESTIONS OR COMMENTS?

CALL TOLL FREE 1-866-933-6337